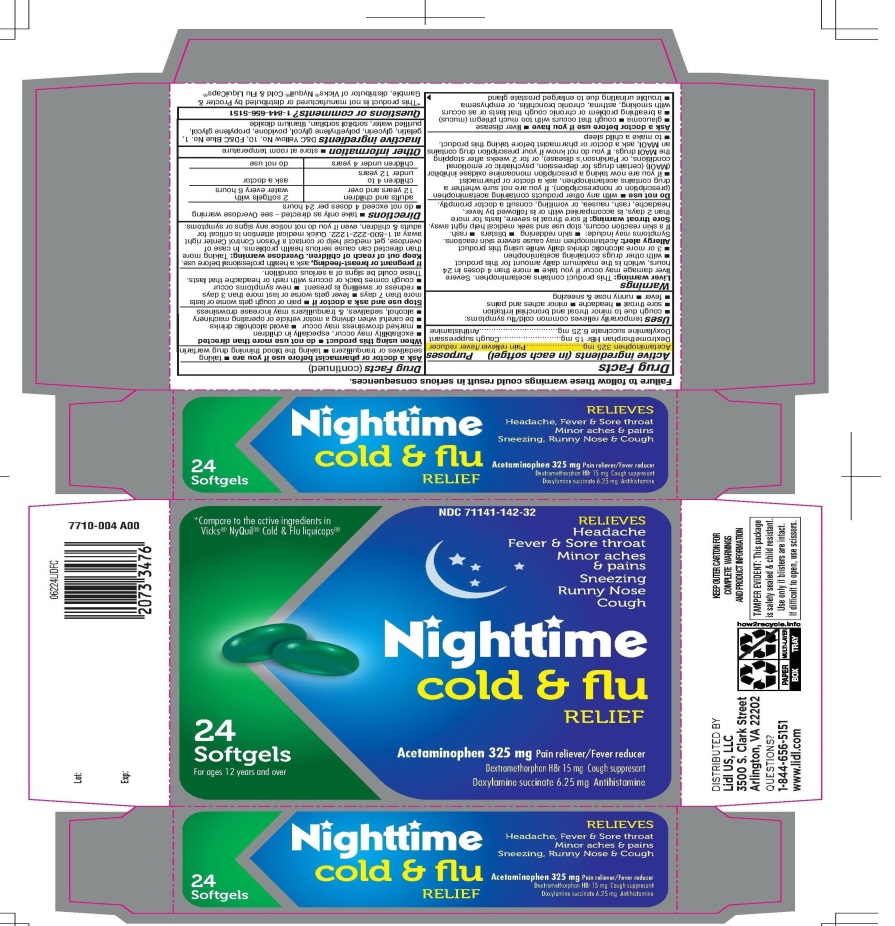 DRUG LABEL: LIDL Nightyime Cold and Flu Relief
NDC: 71141-142 | Form: CAPSULE, LIQUID FILLED
Manufacturer: Lidl US LLC
Category: otc | Type: HUMAN OTC DRUG LABEL
Date: 20210119

ACTIVE INGREDIENTS: ACETAMINOPHEN 325 mg/1 1; DEXTROMETHORPHAN HYDROBROMIDE 15 mg/1 1; DOXYLAMINE SUCCINATE 6.25 mg/1 1
INACTIVE INGREDIENTS: D&C YELLOW NO. 10; FD&C BLUE NO. 1; GELATIN, UNSPECIFIED; GLYCERIN; POLYETHYLENE GLYCOL, UNSPECIFIED; POVIDONE, UNSPECIFIED; PROPYLENE GLYCOL; WATER; SORBITOL; SORBITAN; TITANIUM DIOXIDE

LIDL NIGHTTIME COLD AND FLU RELIEF

Active ingredients (in each softgel)

Acetaminophen 325 mg

Dextromethorphan HBr 15 mg

Doxylamine succinate 6.25 mg

Purpose

Pain reliever/fever reducer

Cough Suppressant

Antihistamine

Uses

temporarily relieves common cold/flu symptoms:
  1. cough due to minor throat and bronchial irritation
  2. sore throat
  3. headache
  4. minor aches and pains
  5. fever
  6. runny nose and sneezing

Warnings

Liver warning: This product contains acetaminophen. Severe liver damage may occur if you take:

- more than 4 doses in 24 hours, which is the maximum daily amount for this product
- with other drugs containing acetaminophen
- 3 or more alcoholic drinks daily while using this product

Allergy alert: Acetaminophen may cause severe skin reactions. Symptoms may include:

- skin reddening
- blisters
- rash

If a skin reaction occurs, stop use and seek medical help right away.

Sore throat warning: If sore throat is severe, persists more than 2 days, is accompanied or followed by fever, headache, rash, nausea, or vomiting, consult a doctor promptly.

Do not use

- with any other product containing acetaminophen (prescription or nonprescription). If you are not sure whether a drug contains acetaminophen, ask a doctor or pharmacist.
- if you are now taking a prescription monoamine oxidase inhibitor (MAOI) (certain drugs for depression, psychiatric or emotional conditions, or Parkinson's disease), or for 2 weeks after stopping the MAOI drug. If you do not know if your prescription drug contains an MAOI, ask a doctor of pharmacist before taking this product.
- to make a child sleep

Ask a doctor before use if you have

- liver disease
- glaucoma
- cough that occurs with too much phlegm (mucus)
- a breathing problem or chronic cough that lasts or as occurs with smoking, asthma, chronic bronchitis or emphysema
- trouble urinating due to an enlarged prostate gland

Ask a doctor or pharmacist before use if you are

- taking sedatives or tranquilizers
- taking the blood thinning drug warfarin

When using this product

- do not use more than directed
- excitability may occur, especially in children
- marked drowsiness may occur
- marked drowsiness may occur
- avoid alcoholic drinks
- be careful when driving a motor vehicle or operating machinery
- alcohol, sedatives & tranquilizers may increase drowsiness

Stop use and ask a doctor if

- pain or cough gets worse or lasts more than 7 days
- fever gets worse or lasts more than 3 days
- redness or swelling is present
- new symptoms occur
- cough comes back or occurs with rash or headache that lasts

These could be signs of a serious condition.

If pregnant or breast-feeding,

ask a health professional before use.

Keep out of reach of children.

Overdose warning: Taking more than directed can cause serious health problems. In case of overdose, get medical help or contact a Poison Control Center right away at 1-800-222-1222. Quick medical attention is critical for adults & children, even if you do not notice any signs or symptoms.

Directions

- take only as directed- see Overdose warning
- do not exceed 4 doses in 24 hours

adults and children 12 years and over | 2 softgels with water every 6 hours
children 4 to under 12 years | ask a doctor
children under 4 years | do not use

Other information

- store at room temperature

Inactive ingredients

D&C yellow No. 10, FD&C Blue No. 1, gelatin, glycerin, polyethylene glycol, povidone, propylene glycol, purified water, sorbitol, sorbitan, titanium dioxide.

Questions or comments?

1-844-656-5151

Principal Display Panel

*Compare to the active ingredients in Vicks® NyQuil® Cold & Flu liquicaps®

NDC 71141-142-32

RELIEVES

Headache

Fever & Sore throat

Minor aches & pains

Sneezing

Runny Nose

Cough

Nighttime Cold & Flue RELIEF

Acetaminophen 325 mg Pain reliever/Fever reducer

Dextromethorphan HBr 15 mg Cough suppressant

Doxylamine succinate 6.25 mg Antihistamine

24 Softgels

For ages 12 years and overs

*This product is not manufactured or distributed by Procter & Gamble, distributor of Vicks® Nyquil® Cold & Flu LiquiCaps®

DISTRIBUTED BY

Lidl US, LLC

3500 S. Clark Street

Arlington, VA 22202

QUESTIONS?

1-844-656-5151

www.lidl.com

KEEP OUTER CARTON FOR COMPLETE WARNINGS AND PRODUCT INFORMATION.

TAMPER EVIDENT: This package is safety sealed & child resistant. Use only if blisters are intact. If difficult to open, use scissors.